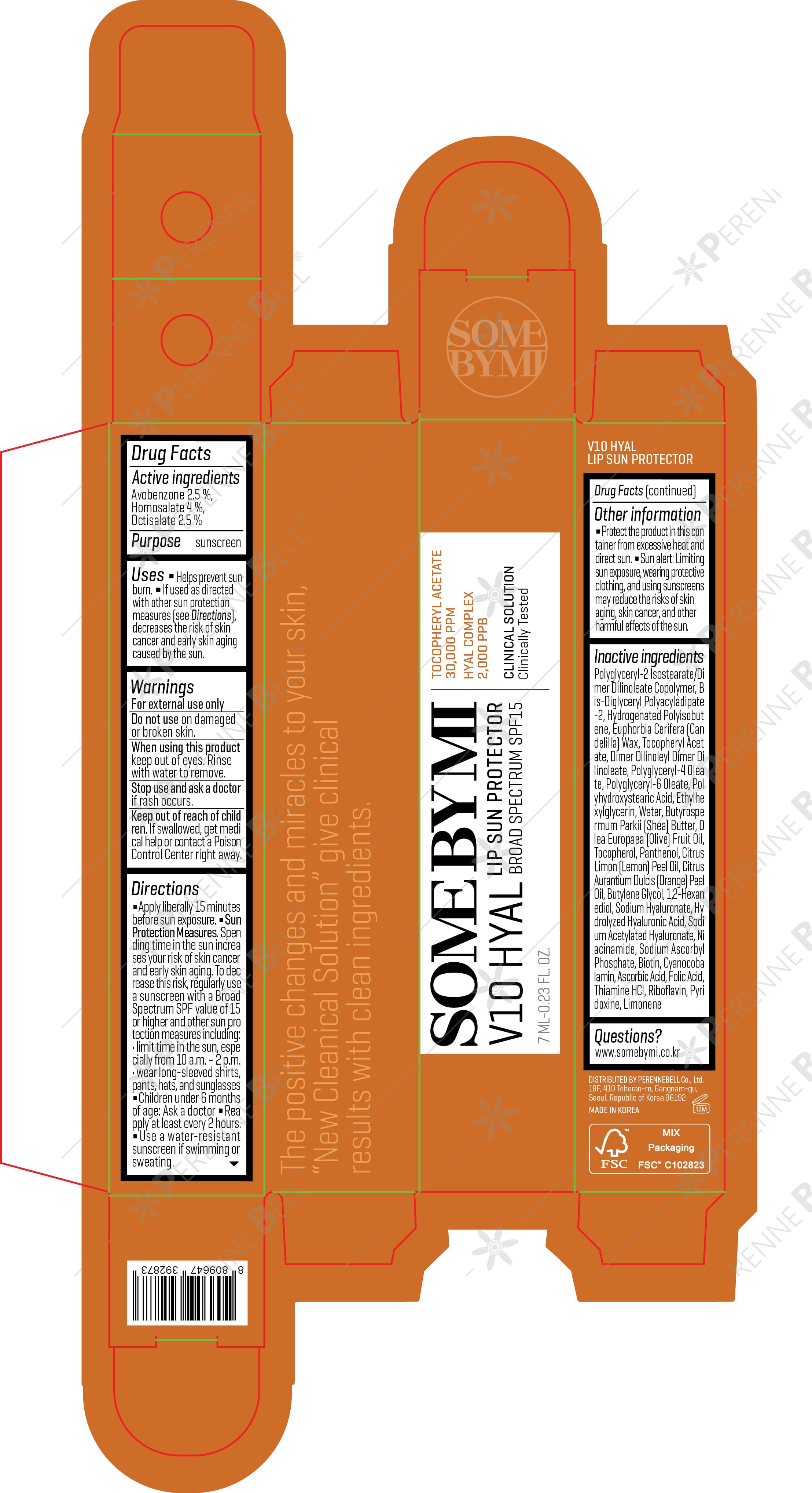 DRUG LABEL: SOME BY MI V10 HYAL LIP SUN PROTECTOR
NDC: 74472-703 | Form: LIPSTICK
Manufacturer: PERENNEBELL Co., Ltd.
Category: otc | Type: HUMAN OTC DRUG LABEL
Date: 20250610

ACTIVE INGREDIENTS: AVOBENZONE 0.175 g/7 mL; OCTISALATE 0.175 g/7 mL; HOMOSALATE 0.28 g/7 mL
INACTIVE INGREDIENTS: BIS-DIGLYCERYL POLYACYLADIPATE-2; TOCOPHEROL; POLYGLYCERYL-4 OLEATE; POLYGLYCERYL-6 OLEATE; ALPHA-TOCOPHEROL ACETATE; ETHYLHEXYLGLYCERIN; BUTYROSPERMUM PARKII (SHEA) BUTTER; THIAMINE HCL; PANTHENOL; SODIUM HYALURONATE; FOLIC ACID; RIBOFLAVIN; 1,2-HEXANEDIOL; POLYHYDROXYSTEARIC ACID STEARATE; SODIUM ACETYLATED HYALURONATE; EUPHORBIA CERIFERA (CANDELILLA) WAX; CITRUS LIMON (LEMON) PEEL OIL; CITRUS AURANTIUM DULCIS (ORANGE) PEEL OIL; PYRIDOXINE; NIACINAMIDE; SODIUM ASCORBYL PHOSPHATE; CYANOCOBALAMIN; HYDROGENATED POLYISOBUTENE (450 MW); WATER; OLEA EUROPAEA (OLIVE) FRUIT OIL; BUTYLENE GLYCOL; DIMER DILINOLEYL DIMER DILINOLEATE; POLYGLYCERYL-2 TRIISOSTEARATE; HYALURONIC ACID; ASCORBIC ACID; BIOTIN; LIMONENE, (+)-

SOME BY MI V10 HYAL LIP SUN PROTECTOR

Active ingredients

Avobenzone 2.5 %
Homosalate 4 %
Octisalate 2.5 %

Purpose

sunscreen

Uses

■ Helps prevent sun burn. ■ If used as directed with other sun protection measures (see Directions), decreases the risk of skin cancer and early skin aging caused by the sun.

Warnings

For external use only

Do not use

on damaged or broken skin.

When using this product

keep out of eyes. Rinse with water to remove.

Stop use and ask a doctor

if rash occurs

Keep out of reach of children.

If swallowed, get medical help or contact a Poison Control Center right away.

Directions

■ Apply liberally 15 minutes before sun exposure.
■ Sun Protection Measures. Spending time in the sun increases your risk of skin cancer and early skin aging. To decrease this risk, regularly use a sunscreen with a Broad Spectrum SPF value of 15 or higher and other sun protection measures including:
• limit time in the sun, especially from 10 a.m. – 2 p.m.
• wear long-sleeved shirts, pants, hats, and sunglasses
■ Children under 6 months of age: Ask a doctor
■ Reapply at least every 2 hours.
■ Use a water-resistant sunscreen if swimming or sweating.

Other information

■ Protect the product in this container from excessive heat and direct sun. ■ Sun alert: Limiting sun exposure, wearing protective clothing, and using sunscreens may reduce the risks of skin aging, skin cancer, and other harmful effects of the sun.

Inactive ingredients

Polyglyceryl-2 Isostearate/Dimer Dilinoleate Copolymer, Bis-Diglyceryl Polyacyladipate-2, Hydrogenated Polyisobutene, Euphorbia Cerifera (Candelilla) Wax, Tocopheryl Acetate, Dimer Dilinoleyl Dimer Dilinoleate, Polyglyceryl-4 Oleate, Polyglyceryl-6 Oleate, Polyhydroxystearic Acid, Ethylhexylglycerin, Water, Butyrospermum Parkii (Shea) Butter, Olea Europaea (Olive) Fruit Oil, Tocopherol, Panthenol, Citrus Limon (Lemon) Peel Oil, Citrus Aurantium Dulcis (Orange) Peel Oil, Butylene Glycol, 1,2-Hexanediol, Sodium Hyaluronate, Hydrolyzed Hyaluronic Acid, Sodium Acetylated Hyaluronate, Niacinamide, Sodium Ascorbyl Phosphate, Biotin, Cyanocobalamin, Ascorbic Acid, Folic Acid, Thiamine HCl, Riboflavin, Pyridoxine, Limonene

Questions?

www.somebymi.co.kr